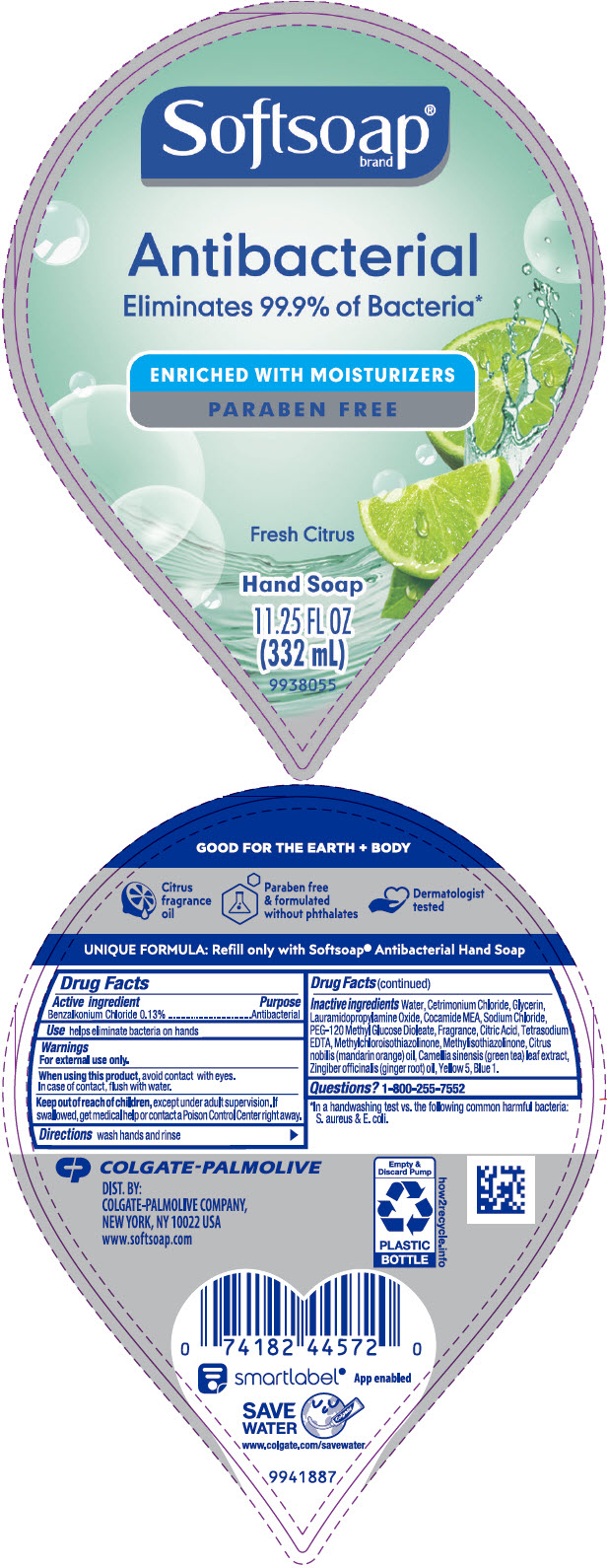 DRUG LABEL: Softsoap Antibacterial with Moisturizers Fresh Citrus LHS
NDC: 35000-099 | Form: LIQUID
Manufacturer: COLGATE PALMOLIVE COMPANY
Category: otc | Type: HUMAN OTC DRUG LABEL
Date: 20200901

ACTIVE INGREDIENTS: BENZALKONIUM CHLORIDE 1.33 mg/1 mL
INACTIVE INGREDIENTS: WATER; CETRIMONIUM CHLORIDE; GLYCERIN; LAURAMIDOPROPYLAMINE OXIDE; COCO MONOETHANOLAMIDE; SODIUM CHLORIDE; PEG-120 METHYL GLUCOSE DIOLEATE; CITRIC ACID MONOHYDRATE; EDETATE SODIUM; METHYLCHLOROISOTHIAZOLINONE; METHYLISOTHIAZOLINONE; MANDARIN OIL; GREEN TEA LEAF; GINGER OIL; FD&C YELLOW NO. 5; FD&C BLUE NO. 1

Softsoap® Antibacterial with Moisturizers Fresh Citrus LHS

Drug Facts

Active ingredient

Benzalkonium Chloride 0.13%

Purpose

Antibacterial

Use

helps eliminate bacteria on hands

Warnings

For external use only

When using this product, avoid contact with eyes.

In case of contact, flush with water.

Keep out of reach of children, except under adult supervision. If swallowed, get medical help or contact a Poison Control Center right away.

Directions

wash hands and rinse

Inactive ingredients

Water, Cetrimonium Chloride, Glycerin, Lauramidopropylamine Oxide, Cocamide MEA, Sodium Chloride, PEG-120 Methyl Glucose Dioleate, Fragrance, Citric Acid, Tetrasodium EDTA, Methylchloroisothiazolinone, Methylisothiazolinone, Citrus nobilis (mandarin orange) oil, Camellia sinensis (green tea) leaf extract, Zingiber officinalis (ginger root) oil, Yellow 5, Blue 1.

Questions?

1-800-255-7552

DIST. BY:
COLGATE-PALMOLIVE COMPANY,
NEW YORK, NY 10022 USA

PRINCIPAL DISPLAY PANEL - 332 mL Bottle Label

Softsoap®
brand

Antibacterial
Eliminates 99.9% of Bacteria*

ENRICHED WITH MOISTURIZERS
PARABEN FREE

Fresh Citrus

Hand Soap

11.25 FL OZ
(332 mL)

9938055